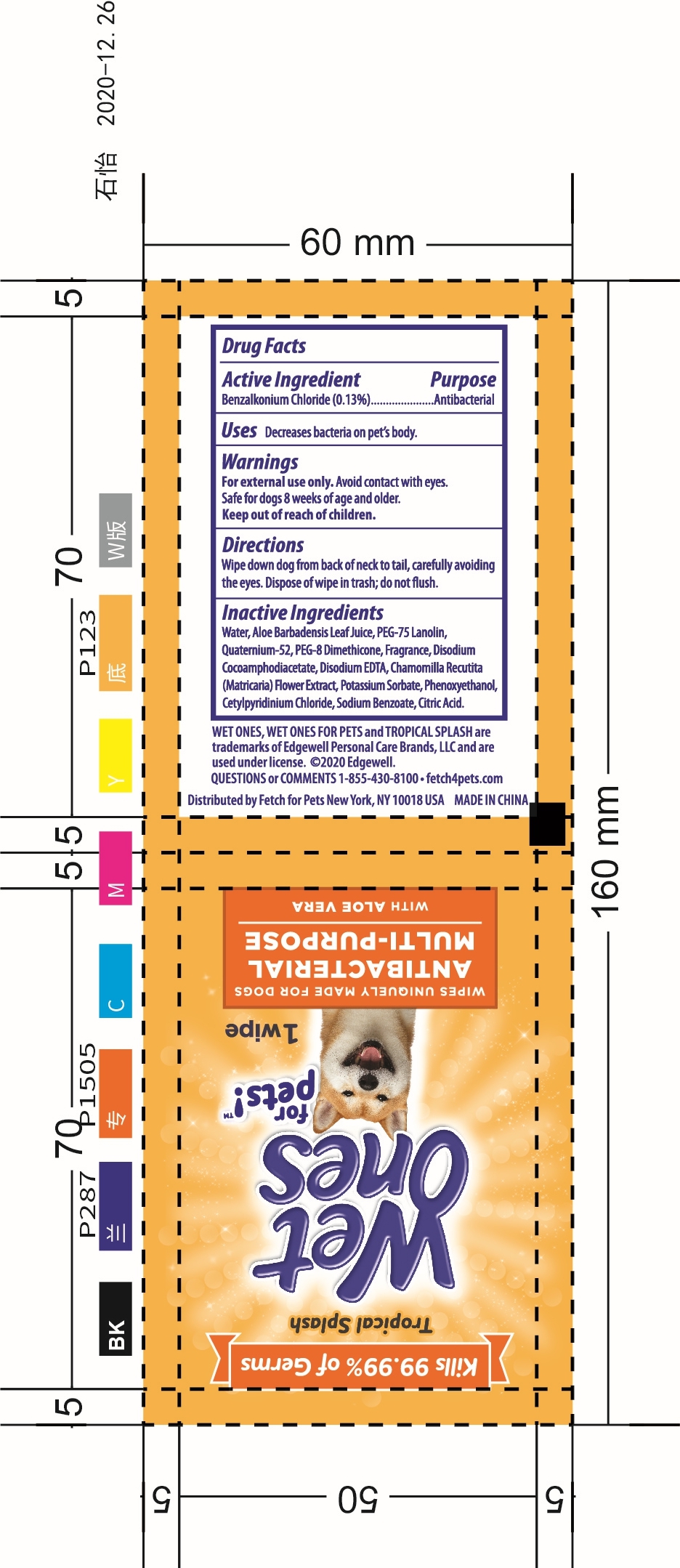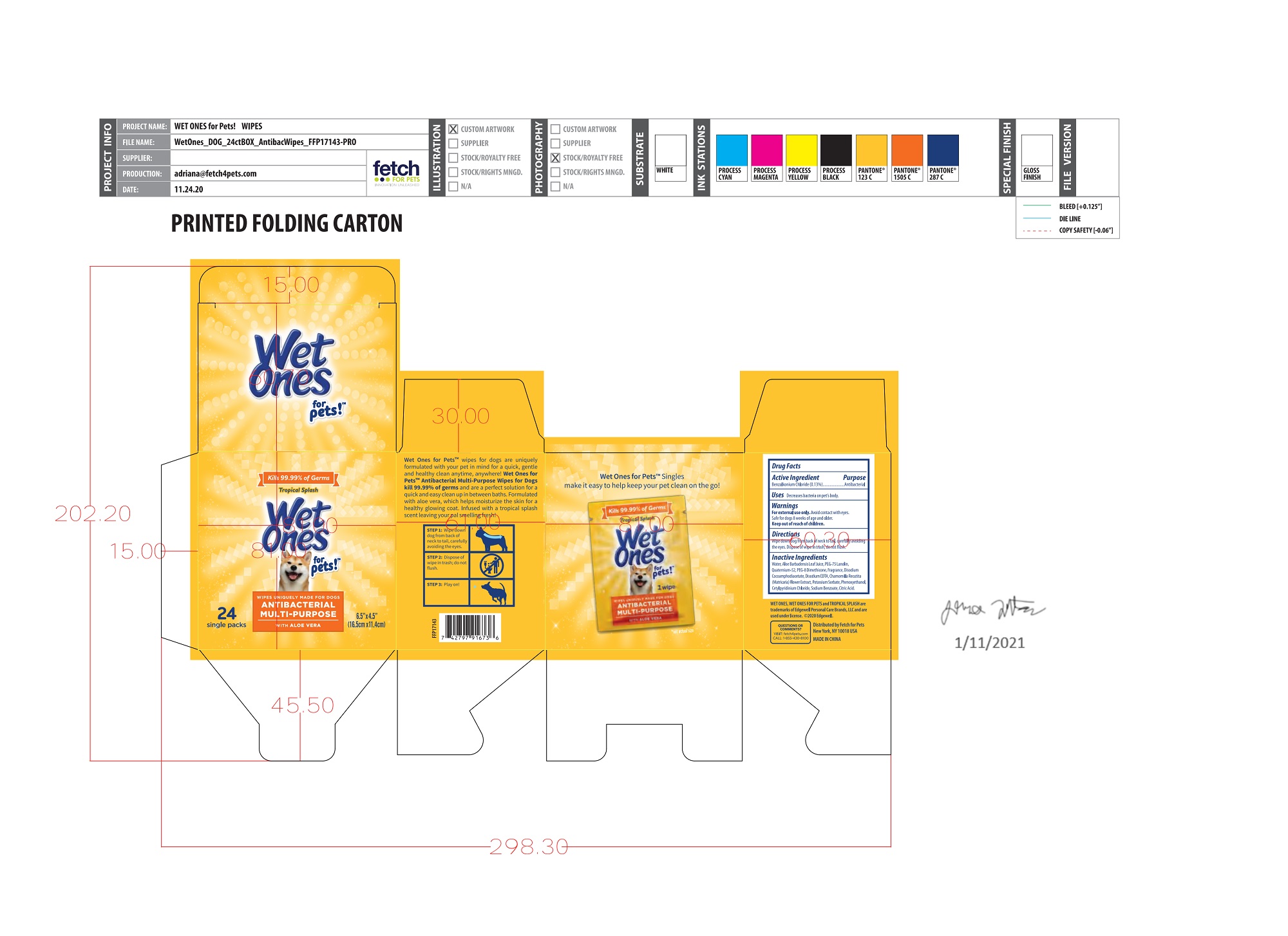 DRUG LABEL: ANTIBACTERIAL MULTI-PURPOSE WIPES
NDC: 77720-021 | Form: CLOTH
Manufacturer: Skaffles Group Limited Liability Company
Category: animal | Type: OTC ANIMAL DRUG LABEL
Date: 20210119

ACTIVE INGREDIENTS: BENZALKONIUM CHLORIDE 0.13 g/100 g
INACTIVE INGREDIENTS: WATER; PEG-75 LANOLIN; QUATERNIUM-52; ALOE VERA LEAF; PEG-8 DIMETHICONE; CHAMOMILE; SODIUM BENZOATE; DISODIUM COCOAMPHODIACETATE; DISODIUM EDTA-COPPER; POTASSIUM SORBATE; PHENOXYETHANOL; CETYLPYRIDINIUM CHLORIDE; CITRIC ACID ACETATE

Active Ingredient

Benzalkonium Chloride 0.13%

USE

Decreases Bacteria on pet]s body.

Warning

For external use only.

Avoid Contact with eyes. Safe for dogs 8 weeks of age and older.

Keep out of reach of children.

Directions

Wipe down dog from back of neck to tail,carefully avoiding the eyes.

didpose of wipe in trash ,do not flush

Inactive ingredients

Water,Aloe Barbadensis Leaf Juice,PEG-75 Lanolin,Quaternium-52,PEG-8 Dimethicone, Fragrance, DisodiumCocoamphodiacetate, Disodium EDTA,Chamomilla Recutita(Matricaria)Flower Extract, Potassium Sorbate, Phenoxyethanol,Cetylpyridinium Chloride, Sodium Benzoate, Citric Acid.